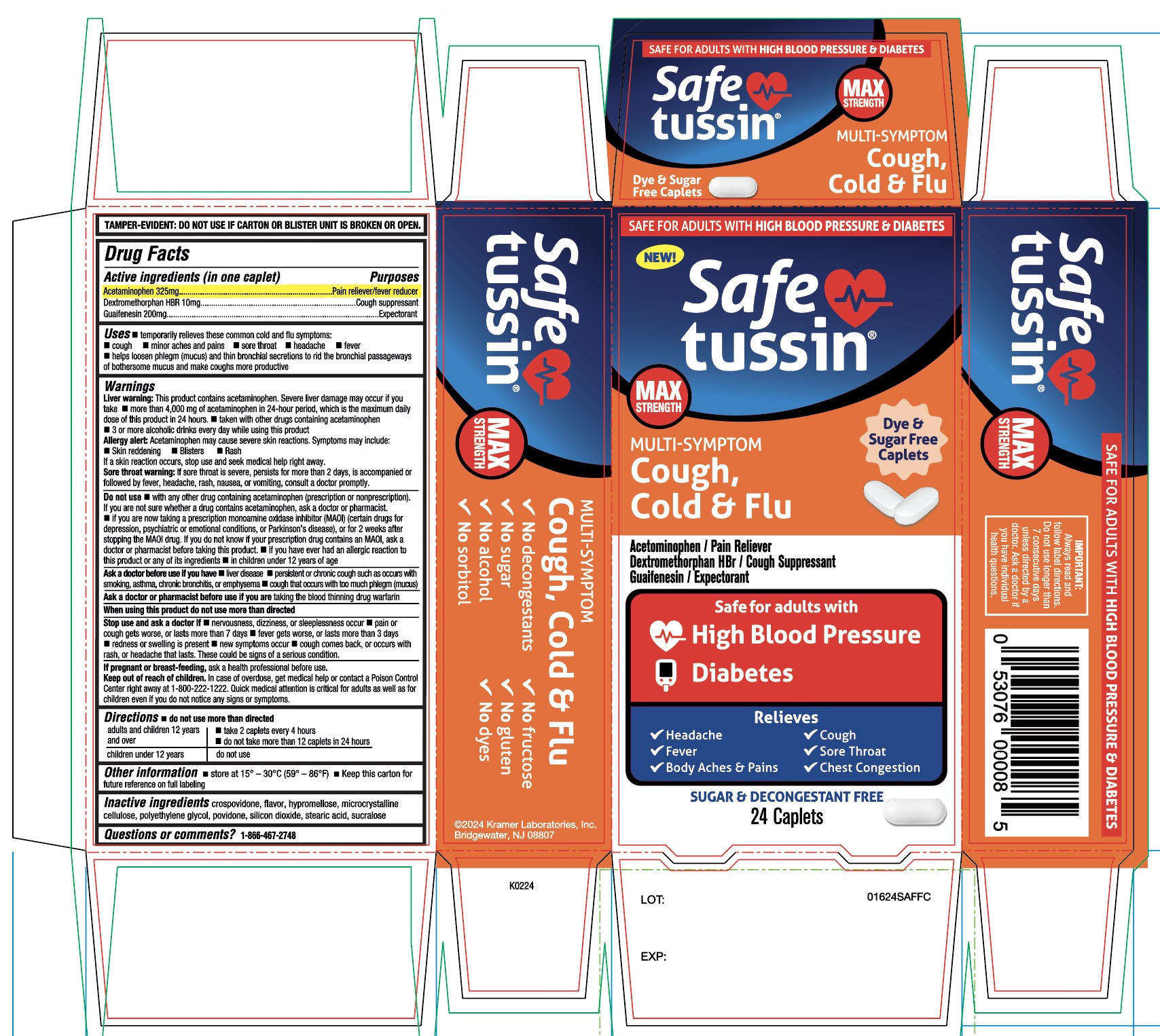 DRUG LABEL: SAFETUSSIN MAX STRENGTH MS
NDC: 55505-230 | Form: TABLET
Manufacturer: KRAMER LABORATORIES
Category: otc | Type: HUMAN OTC DRUG LABEL
Date: 20251223

ACTIVE INGREDIENTS: ACETAMINOPHEN 325 mg/1 1; DEXTROMETHORPHAN HYDROBROMIDE 10 mg/1 1; GUAIFENESIN 200 mg/1 1
INACTIVE INGREDIENTS: CROSPOVIDONE (120 .MU.M); HYPROMELLOSE 2208 (100 MPA.S); MICROCRYSTALLINE CELLULOSE; POLYETHYLENE GLYCOL, UNSPECIFIED; POVIDONE, UNSPECIFIED; SILICON DIOXIDE; STEARIC ACID; SUCRALOSE

SAFETUSSIN MS Cough, Cold & Flu

Drug Facts

ACTIVE INGREDIENT

Active ingredients (in each caplet) | Purpose
Acetaminophen 325 mg | Pain reliever/fever reducer
Dextromethorphan HBr 10 mg | Cough suppressant
Guaifenesin 200 mg | Expectorant

Uses

- temporarily relieves common cold and flu symptoms:
- cough
- sore throat
- headache
- minor aches and pains
- fever
- helps loosen phlegm (mucus) and thin bronchial secretions to get rid the bronchial passageways of bothersome mucus and make coughs more productive

Warnings

Liver warning

This product contains acetaminophen. Severe liver damage may occur if you take

- more than 4000mg of acetaminophen in 24 hours, which is the maximum daily amount for this product in 24 hours
- taken with other drugs containing acetaminophen
- 3 or more alcoholic drinks every day while using this product

Allergy Alert: Acetaminophen may cause severe skin reactions.
Symptoms may include:

- Skin reddening
- Blisters
- Rash

If a skin reaction occurs, stop use and seek medical help right away

Sore throat warning

If sore throat is severe, persists for more than 2 days, is accompanied or followed by fever, headache, rash, nausea, or vomiting, consult a doctor promptly.

Do not use

- with any other drug containing acetaminophen (prescription or nonprescription). If you are not sure whether a drug contains acetaminophen, ask a doctor or pharmacist.
- if you are now taking a prescription monoamine oxidase inhibitor (MAOI) (certain drugs for depression, psychiatric or emotional conditions, or Parkinson's disease), or for 2 weeks after stopping the MAOI drug. If you do not know if your prescription drug contains an MAOI, ask a doctor or pharmacist before taking this product.
- If you have ever had an allergic reaction to this product r any of its ingredients
- In children under 12 years of age

Ask a doctor before use if you have

- liver disease
- cough that occurs with too much phlegm (mucus)
- persistent or chronic cough such as occurs with smoking, asthma, chronic bronchitis or emphysema

Ask a doctor or pharmacist before use if you are

- taking the blood thinning drug warfarin

When using this product

- Do not use more than as directed

Stop use and ask a doctor if

- nervousness, dizziness, or sleeplessness occur
- pain or cough gets worse or lasts more than 7 days
- fever gets worse or lasts more than 3 days
- redness or swelling is present
- new symptoms occur
- cough comes back or occurs with rash or headache that lasts.
  These could be signs of a serious condition.

PREGNANCY OR BREAST FEEDING

If pregnant or breast-feeding, ask a health professional before use.

Keep out of reach of children.

Directions

- do not use more than directed.

adults & children 12 years & over | Take 2 caplets every 4 hours (do not take more than 12 caplets in 24 hours)
children under 12 years of age | do not use

Other information

-
  - store at 15°-30°C (59° - 86°F).
  - Keep this carton for future reference on full labeling.

Inactive ingredients

Crospovidone, flavor, Hypromellose, microcrystalline cellulose, polyethylene glycol, povidone, silicon dioxide, stearic acid, sucralose.

Questions or comments

1-866-467-2748

PRINCIPAL DISPLAY PANEL - 236 ml Bottle Label

SAFE FOR ADULTS WITH HIGH BLOOD PRESSURE & DIABETES

NDC 55505-230-24

Safetussin®

MAX STRENGTH

MULTI-SYMPTOM

Cough, Cold & Flu

Acetaminophen / Pain Reliever

Dextromethorphan HBr / Cough Suppressant

Guaifenesin / Expectorant

Safe for adults with

High Blood Pressure

Diabetes

Relieves

- Headache
- Fever
- Sore Throat
- Body Aches & Pains
- Chest Congestion
- Cough

Safetussin® contains:

No decongestants

No Sugar

No Alcohol

No sorbitol

No fructose

No gluten

No dyes

SUGAR & DECONGESTANT FREE

24 Caplets

Always read and follow label directions. Do not use longer than 7 consecutive days unless directed by a doctor. Ask a doctor if you have individual health questions.

©2024 Kramer Laboratories, Inc. Bridgewater, NJ 08807